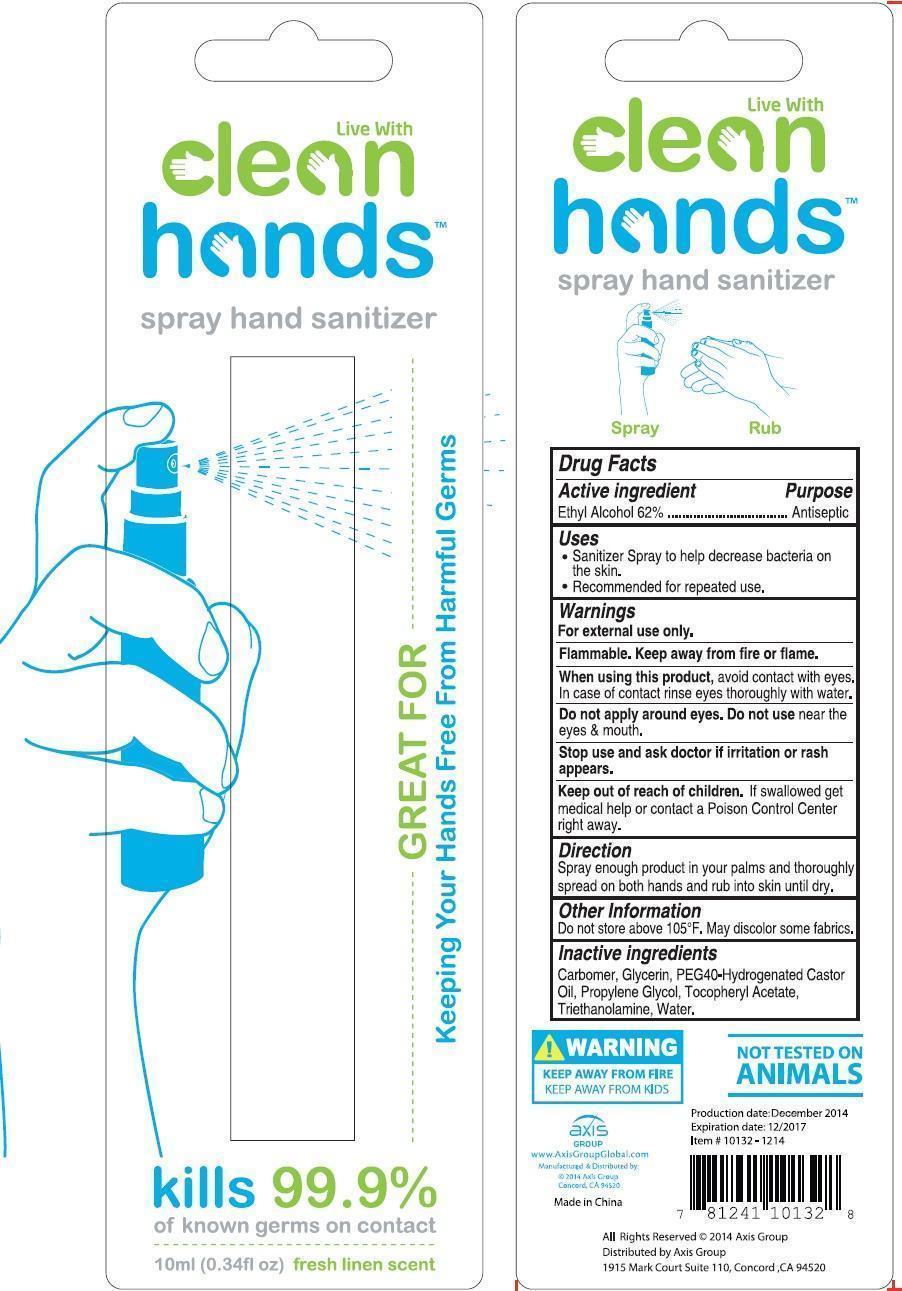 DRUG LABEL: Clean hand sanitizer
NDC: 58180-210 | Form: SPRAY
Manufacturer: Bicooya Cosmetics Limited
Category: otc | Type: HUMAN OTC DRUG LABEL
Date: 20141209

ACTIVE INGREDIENTS: ALCOHOL 62 mL/100 mL
INACTIVE INGREDIENTS: ALOE; FD&C BLUE NO. 1; FD&C YELLOW NO. 5; GLYCERIN; ISOPROPYL ALCOHOL; POLYOXYL 40 HYDROGENATED CASTOR OIL; PROPYLENE GLYCOL; TROLAMINE; WATER

Drug Facts

Active Ingredient

Ethyl Alcohol 62%

Purpose
Antiseptic

INDICATIONS AND USAGE

Uses • sanitizer spray to help decrease bacteria on the skin

•recommended for repeated use.

WARNINGS

Warnings •Flammable. • Keep away from fire or flame. •For external use only

When using this product •avoid contact with eyes • in case of contact, rinse eyes throughtly with water

•do not apply around eyes, do not use near the eyes and mouth.

Keep out of reach of children. if sweallowede, get medical help or contact a Poison Control Center right away.

Other information • do not store above 105F. May discolor some fabrics.

DOSAGE AND ADMINISTRATION

Directions • spray enough product in your palms and thoroughly spread on both hands and rub into skin until dry.

INACTIVE INGREDIENT

Inactive ingredients aloe barbadensis gel, carbomer, fragrance, FD&C blue no. 1, FD&C yellow no.5, glycerin, isopropyl alcohol, PEG-40 hydrogenated castor oil, propylene glycol, triethanolamine, water

Package Label